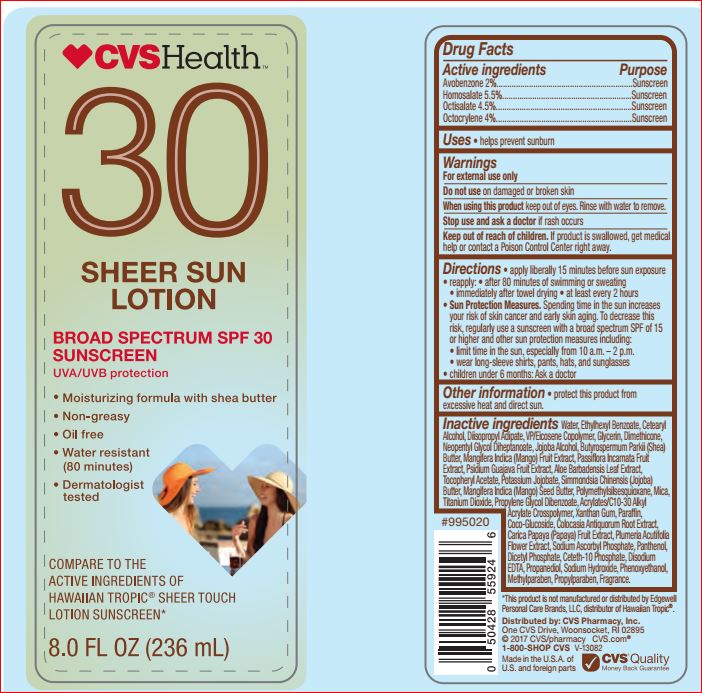 DRUG LABEL: Sheer Sunscreen SPF 30
NDC: 69842-841 | Form: LOTION
Manufacturer: CVS
Category: otc | Type: HUMAN OTC DRUG LABEL
Date: 20171211

ACTIVE INGREDIENTS: Avobenzone 2 g/100 mL; Homosalate 5.5 g/100 mL; Octisalate 4.5 g/100 mL; Octocrylene 4 g/100 mL
INACTIVE INGREDIENTS: Water; 2-ETHYLHEXYL BENZOATE; CETOSTEARYL ALCOHOL; Diisopropyl Adipate; VINYLPYRROLIDONE/EICOSENE COPOLYMER; Glycerin; Dimethicone; Neopentyl Glycol Diheptanoate; SHEA BUTTER; MANGO JUICE; PASSIFLORA INCARNATA FRUIT; GUAVA; ALOE VERA LEAF; .ALPHA.-TOCOPHEROL ACETATE; JOJOBA BUTTER; MANGIFERA INDICA SEED BUTTER; Mica; Titanium Dioxide; Propylene Glycol Dibenzoate; Xanthan Gum; Paraffin; Coco Glucoside; COLOCASIA ESCULENTA ROOT; PAPAYA; PLUMERIA RUBRA FLOWER; Sodium Ascorbyl Phosphate; Panthenol; DIHEXADECYL PHOSPHATE; Ceteth-10 Phosphate; EDETATE DISODIUM; Propanediol; Sodium Hydroxide; Phenoxyethanol; Methylparaben; Propylparaben; CARBOMER INTERPOLYMER TYPE A (ALLYL SUCROSE CROSSLINKED)

DRug Facts

Active ingredients Purpose
Avobenzone 2.00%..........................Sunscreen
Homosalate 5.50%...........................Sunscreen
Octisalate 4.50%..............................Sunscreen
Octocrylene 4.00%...........................Sunscreen

INDICATIONS AND USAGE

Use • helps prevent sunburn

Warnings
For external use only
Do not use on damaged or broken skin
When using this product keep out of eyes. Rinse with water to remove.
Stop use and ask a doctor if rash occurs

Keep out of reach of children.

If product is swallowed, get medical help or contact a Poison Control Center right away

Directions
• Apply liberally 15 minutes before sun exposure
• Use a water resistant sunscreen if swimming
or sweating
• Reapply at least every 2 hours
• Children under 6 months: Ask a doctor
• Sun Protection Measures. Spending time in
the sun increases your risk of skin cancer and
early skin aging. To decrease this risk, regularly
use a sunscreen with a broad spectrum SPF
of 15 or higher and other sun protection
measures including: • limit time in the sun,
especially from 10 a.m. – 2 p.m. • wear
long-sleeve shirts, pants, hats, and sunglasses

Inactive ingredients

Water
Ethylhexyl Benzoate
Cetearyl Alcohol
Diisopropyl Adipate
VP/Eicosene Copolymer
Glycerin
Dimethicone
Neopentyl Glycol Diheptanoate

Jojoba Alcohol
Butyrospermum Parkii (Shea) Butter
Mangifera Indica (Mango) Fruit Extract
Passiflora Incarnata Fruit Extract
Psidium Guajava Fruit Extract
Aloe Barbadensis Leaf Extract
Tocopheryl Acetate
Potassium Jojobate
Simmondsia Chinensis (Jojoba) Butter
Mangifera Indica (Mango) Seed Butter
Polymethylsilsesquioxane
Mica
Titanium Dioxide
Propylene Glycol Dibenzoate
Acrylates/C10-30 Alkyl Acrylate Crosspolymer
Xanthan Gum
Paraffin
Coco-Glucoside
Colocasia Antiquorum Root Extract
Carica Papaya (Papaya) Fruit Extract
Plumeria Acutifolia Flower Extract

Sodium Ascorbyl Phosphate
Panthenol
Dicetyl Phosphate
Ceteth-10 Phosphate
Disodium EDTA
Propanediol
Sodium Hydroxide
Phenoxyethanol
Methylparaben
Propylparaben
Fragrance